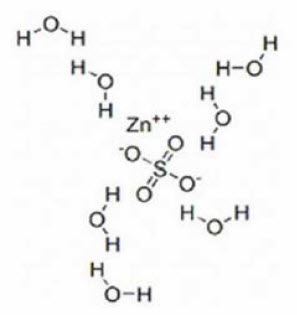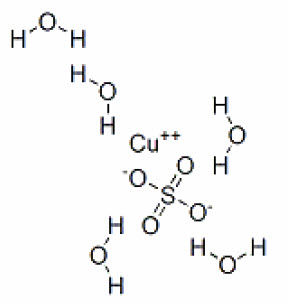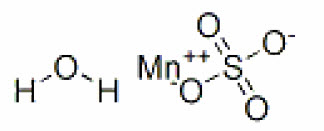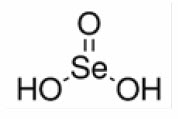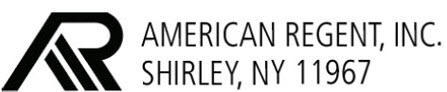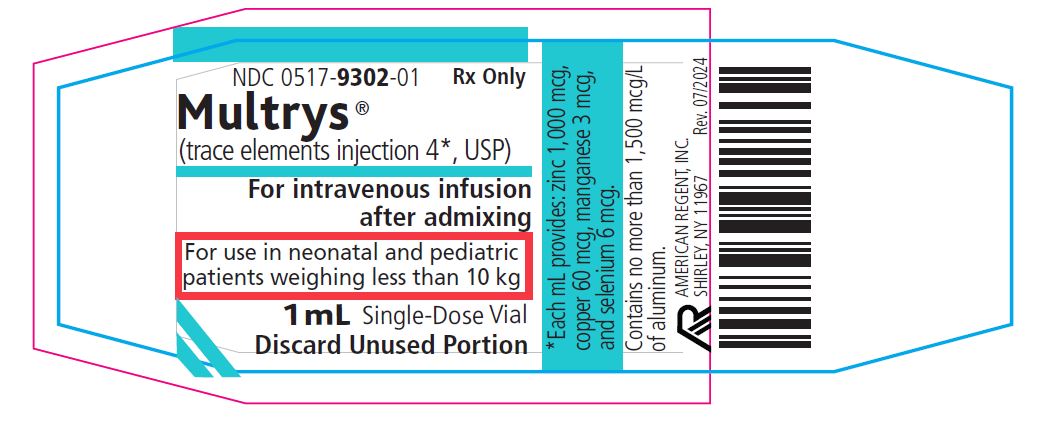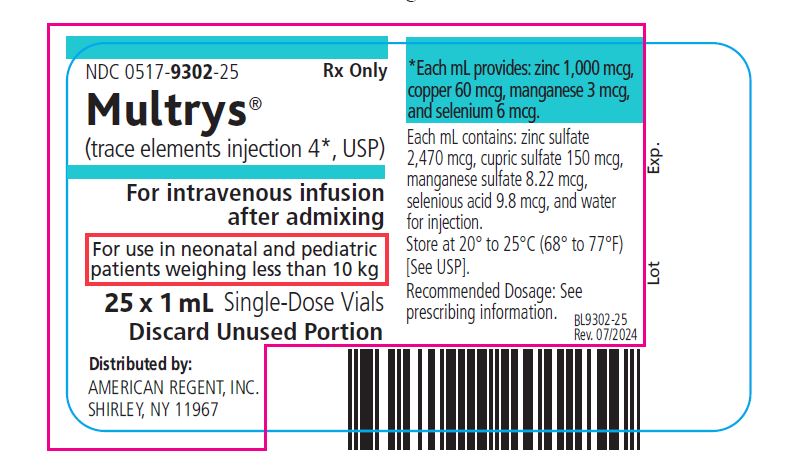 DRUG LABEL: Multrys
NDC: 0517-9302 | Form: INJECTION, SOLUTION
Manufacturer: American Regent, Inc.
Category: prescription | Type: HUMAN PRESCRIPTION DRUG LABEL
Date: 20240701

ACTIVE INGREDIENTS: ZINC SULFATE 2470 ug/1 mL; CUPRIC SULFATE 150 ug/1 mL; MANGANESE SULFATE 8.22 ug/1 mL; SELENIOUS ACID 9.8 ug/1 mL
INACTIVE INGREDIENTS: WATER

HIGHLIGHTS OF PRESCRIBING INFORMATION

These highlights do not include all the information needed to use MULTRYS® safely and effectively. See full prescribing information for MULTRYS® .
MULTRYS® (trace elements injection 4*) for intravenous use
Initial U.S. Approval: 2020

1 INDICATIONS AND USAGE

Multrys is a combination of trace elements (zinc sulfate, cupric sulfate, manganese sulfate, and selenious acid) indicated in neonatal and pediatric patients weighing less than 10 kg as a source of zinc, copper, manganese, and selenium for parenteral nutrition when oral or enteral nutrition is not possible, insufficient, or contraindicated. (1)

2 DOSAGE AND ADMINISTRATION

- Single-dose vial, for admixture use only. (2.1)
- See full prescribing information for information on preparation, administration and general dosing considerations. (2.1, 2.2, 2.3, 2.4)
  Recommended Dosage
- Each mL of Multrys provides zinc 1,000 mcg, copper 60 mcg, manganese 3 mcg, and selenium 6 mcg. (2.5)
- Multrys is recommended only for pediatric patients who require supplementation with all four of the individual trace elements (i.e., zinc, copper, manganese, and selenium) to meet daily requirements. (2.5)
- Pediatric Patients 0.4 kg to 0.59 kg: The total recommended dosage of Multrys is 0.2 mL every other day.Daily supplementation of Zinc Sulfate, Cupric Chloride and Selenious Acid will be needed to meet daily requirements. (2.5)
- Pediatric Patients 0.6 kg to 10 kg: The recommended dosage of Multrys is 0.3 mL/kg/day rounded to the nearest 0.1 mL for up to a maximum of 1 mL per day. The recommended volume of Multrys to be added to parenteral nutrition ranges from 0.2 mL per day to 1 mL per day based on body weight. (2.5)
- Multrys is not recommended for patients who may require a lower dosage of one or more of the individual trace elements. (2.5)
- Monitor trace element concentrations in blood during long-term administration of parenteral nutrition. (2.5)

3 DOSAGE FORMS AND STRENGTHS

Injection: Each mL contains zinc 1,000 mcg, copper 60 mcg, manganese 3 mcg, and selenium 6 mcg in a 1 mL, single-dose vial. (3)

4 CONTRAINDICATIONS

Hypersensitivity to zinc or copper (4, 5.7)

5 WARNINGS AND PRECAUTIONS

- Pulmonary Embolism due to Pulmonary Vascular Precipitates: If signs of pulmonary distress occur, stop the infusion and initiate a medical evaluation. (5.1)
- Vein Damage and Thrombosis:Solutions with osmolarity of 900 mOsmol/L or more must be infused through a central catheter. (2.1, 5.2)
- Neurologic Toxicity with Manganese:Monitor for clinical signs and symptoms of neurotoxicity, whole blood manganese concentrations, and liver function tests in patients receiving long-term Multrys.Discontinue Multrys and consider brain magnetic resonance imaging (MRI) if toxicity is suspected. (5.3)
- Hepatic Accumulation of Copper and Manganese:Assess for development of hepatic accumulation.Monitor concentrations of copper and manganese in patients with cholestasis or cirrhosis receiving Multrys long-term. (5.4)
- Aluminum Toxicity: Increased risk in patients with renal impairment, including preterm infants. (5.5)
- Monitoring and Laboratory Tests: Monitor zinc, copper, and selenium serum concentrations, whole blood manganese concentration, fluid and electrolyte status, serum osmolarity, blood glucose, liver and kidney function, blood count, and coagulation parameters. (5.6, 2.4)
- Hypersensitivity Reactions with Zinc and Copper: If reactions occur, discontinue Multrys and initiate appropriate medical treatment. (5.7)

6 ADVERSE REACTIONS

This section intentionally left blank. (6)
To report SUSPECTED ADVERSE REACTIONS, contact American Regent, Inc. at 1-800-734-9236 or FDA at 1-800-FDA-1088 or www.fda.gov/medwatch.

8 USE IN SPECIFIC POPULATIONS

This section intentionally left blank. (8)

FULL PRESCRIBING INFORMATION

1 INDICATIONS AND USAGE

Multrys is indicated in neonatal and pediatric patients weighing less than 10 kg as a source of zinc, copper, manganese, and selenium for parenteral nutrition when oral or enteral nutrition is not possible, insufficient, or contraindicated.

2 DOSAGE AND ADMINISTRATION

2.1 Important Administration Information

Multrys is supplied as a single-dose vial for admixture use only. Prior to administration, Multrys must be transferred to a separate parenteral nutrition container and used as an admixture in parenteral nutrition solution.

The final parenteral nutrition solution is for intravenous infusion into a central or peripheral vein. The choice of a central or peripheral venous route should depend on the osmolarity of the final infusate. Solutions with osmolarity of 900 mOsmol/L or greater must be infused through a central catheter [see Warnings and Precautions (5.2)].

2.2 Preparation and Administration Instructions

- Multrys is for admixture use only.Prior to administration, Multrys must be prepared and used as an admixture in parenteral nutrition solution.
- Add Multrys to the parenteral nutrition solution in a suitable work area such as a laminar flow hood (or an equivalent clean air compounding area).The key factor in the preparation is careful aseptic technique to avoid inadvertent touch contamination during mixing of solutions and addition of other nutrients.
- Inspect the parenteral nutrition solution containing Multrys for particulate matter before admixing, after admixing, and prior to administration.

2.3 Preparation Instructions for Admixing Using a Parenteral Nutrition Container

- Inspect Multrys single-dose vial for particulate matter.
- Transfer Multrys to the parenteral nutrition container after the admixture of amino acids, dextrose, lipid emulsion (if added), and electrolyte solutions is prepared.
- Because additives may be incompatible, evaluate all additions to the parenteral nutrition container for compatibility and stability of the resulting preparation.Consult with a pharmacist, if available.For introducing additives to the parenteral nutrition container, use aseptic technique.
- An interaction may occur between cupric ion and ascorbic acid; therefore, multivitamin additives should be added to the admixed parenteral nutrition solution shortly before infusion.
- Inspect the final parenteral nutrition solution containing Multrys to ensure that:
  - Precipitates have not formed during mixing or addition of additives.
  - The emulsion has not separated, if lipid emulsion has been added.Separation of the emulsion can be visibly identified by a yellowish streaking or the accumulation of yellowish droplets in the admixed emulsion.
  - Discard if any precipitates are observed.

Stability and Storage

- Single dose vial.Discard any unused portion.
- Penetrate vial closure only one time with a suitable sterile transfer device or dispensing set that allows measured dispensing of the contents.
- Transfer Multrys to the parenteral nutrition container promptly after removal from the vial. Discard any remaining drug.
- Use parenteral nutrition solutions containing Multrys promptly after mixing.Any storage of the admixture should be under refrigeration from 2ºC to 8ºC (36ºF to 46ºF) and limited to a period of no longer than 9 days.After removal from refrigeration, use promptly and complete the infusion within 24 hours. Discard any remaining admixture.
- Protect the parenteral nutrition solution from light.

2.4 Overview of Dosing

- Prior to administration of parenteral nutrition solution containing Multrys, correct severe fluid, electrolyte, and acid-base disorders.
- The dosage of the final parenteral nutrition solution containing Multrys must be based on the concentrations of all components in the solution, the patient’s clinical condition, nutritional requirements, and the contribution of oral or enteral intake.
- Monitor fluid and electrolyte status during treatment use of Multrys and adjust the parenteral nutrition solution as needed.

2.5 Recommended Dosage in Pediatric Patients and Monitoring Considerations

Multrys is a fixed-combination product. Each mL of Multrys provides zinc 1,000 mcg, copper 60 mcg, manganese 3 mcg, and selenium 6 mcg.

Recommended Dosage for Pediatric Patients Weighing 0.4 kg to 0.59 kg

- The total recommended dosage of Multrys is 0.2 mL every other day.
- Daily supplementation of Zinc, Copper, and Selenium will be needed to meet daily requirements (See Table 2 below).

Recommended Dosage for Pediatric Patients Weighing 0.6 kg to less than 10 kg

- The recommended dosage of Multrys is 0.3 mL/kg/day rounded to nearest 0.1 mL for up to a maximum of 1 mL per day.
- The recommended volume of Multrys to be added to parenteral nutrition ranges from 0.2 mL per day to 1 mL per day based on body weight, see Table 1 below.

Table 1. Recommended Daily Volume of Multrys and Corresponding Amount of Each Trace Element (mcg)

Body Weight | Recommended Daily Volume | Amount of Trace Element Provided by the Corresponding Multrys Volume
Body Weight | Recommended Daily Volume | Zinc mcg | Copper mcg | Manganese mcg | Selenium mcg
0.6 kg to 0.8 kg | 0.2 mL | 200 | 12 | 0.6 | 1.2
0.9 kg to 1.1 kg | 0.3 mL | 300 | 18 | 0.9 | 1.8
1.2 kg to 1.4 kg | 0.4 mL | 400 | 24 | 1.2 | 2.4
1.5 kg to 1.7 kg | 0.5 mL | 500 | 30 | 1.5 | 3
1.8 kg to 2 kg | 0.6 mL | 600 | 36 | 1.8 | 3.6
2.1 kg to 2.3 kg | 0.7 mL | 700 | 42 | 2.1 | 4.2
2.4 kg to 2.6 kg | 0.8 mL | 800 | 48 | 2.4 | 4.8
2.7 kg to 2.9 kg | 0.9 mL | 900 | 54 | 2.7 | 5.4
3 kg to 9.9 kg | 1 mL | 1,000 | 60 | 3 | 6

Additional Trace Element Supplementation with Multrys

Multrys is recommended only for pediatric patients who require supplementation with all four of the individual trace elements (i.e., zinc, copper, manganese and selenium).

- To determine the additional amount of supplementation that is needed, compare the calculated daily recommended dosage based on the body weight of the patient to the amount of each trace element provided by Multrys and enteral nutrition sources.

Table 2: Daily Requirement for Trace Element Supplementation for Pediatric Patients

Trace Element | Patient Weight (kg) | Daily Requirement*
Zinc | Less than 3 kg | 400 mcg/kg/day
Zinc | 3 kg to 5 kg | 250 mcg/kg/day
Zinc | 5 to 10 kg | 100 mcg/kg/day
Copper | - | 20 mcg/kg/day
Selenium | - | 2 mcg/kg/day
Manganese** | - | 1 mcg/kg/day

*Multrys is not recommended for pediatric patients who may require a lower dosage of one or more of these individual trace elements.

**Avoid additional manganese supplementation with Multrys use. Accumulation of manganese in the brain can occur with long-term administration with higher than the recommended dosage of 1 mcg/kg/day [see Warnings and Precautions (5.3)].

For pediatric patients weighing less than 3 kg, Multrys does not provide the recommended daily dosage of zinc.

- Zinc:For patients weighing less than 3 kg, add Zinc Sulfate to provide total daily recommended dose of 400 mcg/kg/day using parenteral and/or enteral routes of administration.

For pediatric patients weighing 0.4 kg to 0.59 kg and 4 kg to 9.9 kg, Multrys does not provide the recommended daily dosage of copper or selenium.

- Copper:For patients weighing 0.4 to 0.59 kg or 4 kg to 9.9 kg, add Cupric Chloride to provide total daily recommended dose of 20 mcg/kg/day using parenteral and/or enteral routes of administration.
- Selenium: For patients weighing 0.4 to 0.59 kg or 4 kg to 9.9 kg, add Selenious Acid to provide total daily recommended dose of 2 mcg/kg/day using parenteral and/or enteral routes of administration.

Monitoring

- Monitor zinc, copper, and selenium serum concentrations and manganese whole blood concentrations during long-term administration of parenteral nutrition.
- Trace element concentrations may vary depending on the assay used and the laboratory reference range.The collection, processing, and storage of the blood samples should be performed according to the laboratory’s sample requirements for analysis.

3 DOSAGE FORMS AND STRENGTHS

Injection: Each mL of Multrys contains zinc 1,000 mcg, copper 60 mcg, manganese 3 mcg, and selenium 6 mcg in a clear, colorless to slightly blue solution, single-dose vial.

4 CONTRAINDICATIONS

Multrys is contraindicated in patients with hypersensitivity to zinc or copper [see Warnings and Precautions (5.7)].

5 WARNINGS AND PRECAUTIONS

5.1 Pulmonary Embolism due to Pulmonary Vascular Precipitates

Pulmonary vascular precipitates causing pulmonary vascular emboli and pulmonary distress have been reported in patients receiving parenteral nutrition. The cause of precipitate formation has not been determined in all cases; however, in some fatal cases, pulmonary emboli occurred as a result of calcium phosphate precipitates. Precipitation has occurred following passage through an in-line filter; in vivo precipitate formation may also have occurred. If signs of pulmonary distress occur, stop the parenteral nutrition infusion and initiate a medical evaluation. In addition to inspection of the solution [see Dosage and Administration (2.2, 2.3)], the infusion set and catheter should also periodically be checked for precipitates.

5.2 Vein Damage and Thrombosis

Multrys must be prepared and used as an admixture in parenteral nutrition solution. It is not for direct intravenous infusion. In addition, consider the osmolarity of the final parenteral nutrition solution in determining peripheral versus central administration. Solution with an osmolarity of 900 mOsmol/L or greater must be infused through a central catheter [see Dosage and Administration (2.1)]. The infusion of hypertonic nutrient solution into a peripheral vein may result in vein irritation, vein damage, and/or thrombosis. The primary complication of peripheral access is venous thrombophlebitis, which manifests as pain, erythema, tenderness or a palpable cord. Remove the catheter as soon as possible, if thrombophlebitis develops.

5.3 Neurologic Toxicity with Manganese

Pediatric patients on long-term parenteral nutrition receiving manganese at higher than recommended dosages and pediatric patients with cholestatic liver disease have experienced manganese accumulation in the basal ganglia. Some adult patients with brain MRI findings reportedly experienced neuropsychiatric symptoms, including changes in mood or memory, seizures and/or parkinsonian-like tremors, dysarthria, mask-face, and halting gait. Some pediatric patients experienced dystonic movements or seizures. Brain MRI findings and clinical symptoms have also been observed in patients who received manganese at or below the recommended dosage and with normal blood manganese concentrations. Regression of symptoms and brain MRI findings have occurred over weeks to months following discontinuation of manganese in most patients but have not always completely resolved.

Monitor patients receiving long-term parenteral nutrition solutions containing Multrys for neurologic signs and symptoms and routinely monitor whole blood manganese concentrations and liver function tests. In case of suspected manganese toxicity or new neuro-psychiatric manifestations, temporarily discontinue Multrys, check manganese whole blood concentrations, and consider brain MRI evaluation.

Monitor patients receiving Multrys for cholestasis or other biliary liver disease. Consider individual trace element products as an alternative to Multrys in patients with hepatobiliary disease [see Warnings and Precautions (5.4)].

5.4 Hepatic Accumulation of Copper and Manganese

Copper is primarily eliminated in the bile and excretion is decreased in patients with cholestasis and/or cirrhosis. Hepatic accumulation of copper and manganese have been reported in autopsies of patients receiving long-term parenteral nutrition containing copper and manganese at dosages higher than recommended.

Patients with cholestasis and/or cirrhosis receiving parenteral nutrition are at increased risk of manganese brain deposition and neurotoxicity [see Warnings and Precautions (5.3)].

Administration of copper to patients with cholestasis and/or cirrhosis may cause hepatic accumulation of copper. Administration of copper to patients with Wilson disease, an inborn error of copper metabolism with a defect in hepatocellular copper transport, may cause both increased hepatic accumulation of copper and aggravation of the underlying hepatocellular degeneration.

If a patient develops signs or symptoms of hepatobiliary disease during the use of Multrys, obtain serum concentrations of copper and ceruloplasmin as well as manganese whole blood concentrations; consider using individual trace element products in these patients [see Use in Specific Populations (8.6)].

5.5 Aluminum Toxicity

Multrys contains aluminum that may be toxic. Aluminum may reach toxic levels with prolonged parenteral administration if kidney function is impaired. Preterm infants, including preterm neonates, are particularly at risk because their kidneys are immature, and they require large amounts of calcium and phosphate solutions, which contain aluminum.

Research indicates that patients with impaired kidney function, including preterm infants and premature neonates, who receive parenteral levels of aluminum at greater than 4 to 5 mcg/kg/day accumulate aluminum at levels associated with central nervous system and bone toxicity. Tissue loading may occur at even lower rates of administration or lower daily amounts.

Exposure to aluminum from Multrys is not more than 0.45 mcg/kg/day. When prescribing Multrys for use in parenteral nutrition containing other small volume parenteral products, the total daily patient exposure to aluminum from the admixture should be considered and maintained at no more than 5 mcg/kg/day.

5.6 Monitoring and Laboratory Tests

Monitor zinc, copper, and selenium serum concentrations, manganese whole blood concentration, fluid and electrolyte status, serum osmolarity, blood glucose, liver and kidney function, blood count, and coagulation parameters during use of parenteral nutrition containing Multrys [see Dosage and Administration (2.4)].

5.7 Hypersensitivity Reactions with Zinc and Copper

Postmarket safety reporting has identified zinc hypersensitivity in patients receiving zinc-containing insulin products and copper hypersensitivity in women receiving copper-containing intrauterine devices, providing evidence that patients may experience hypersensitivity reactions when exposed to these metals. If hypersensitivity reactions (e.g., pruritis, angioedema, dyspnea, rash, urticaria) occur in patients receiving Multrys in parenteral nutrition, discontinue Multrys, and initiate appropriate medical treatment [see Contraindications (4)].

6 ADVERSE REACTIONS

The following adverse reactions were identified in clinical studies or post-marketing reports. Given that some of these reactions were reported voluntarily from a population of uncertain size, it is not always possible to reliably estimate their frequency or establish a causal relationship to drug exposure.

Adverse reactions with other components of parenteral nutrition solutions:

- Pulmonary embolism due to pulmonary vascular precipitates [see Warnings and Precautions (5.1)]
- Vein damage and thrombosis [see Warnings and Precautions (5.2)]
- Aluminum toxicity [see Warnings and Precautions (5.5)]
  Adverse reactions with the use of trace elements administered parenterally or by other routes of administration:
- Neurologic toxicity with manganese [see Warnings and Precautions (5.3)]
- Hepatic accumulation of copper and manganese [see Warnings and Precautions (5.4)]
- Hypersensitivity reactions with zinc and copper [see Warnings and Precautions (5.7)]

8 USE IN SPECIFIC POPULATIONS

8.4 Pediatric Use

Multrys is approved for use in neonatal and pediatric patients weighing less than 10 kg as a source of zinc, copper, manganese, and selenium for parenteral nutrition when oral or enteral nutrition is not possible, insufficient, or contraindicated. Safety and dosing recommendations in pediatric patients less than 10 kg are based on published literature describing controlled studies of products containing zinc, copper, manganese, and selenium [see Dosage and Administration (2.5)].

8.6 Hepatic Impairment

Copper is primarily excreted in the bile. Excretion is decreased in patients with cholestasis and/or cirrhosis. Manganese is presumed to be excreted in bile [see Clinical Pharmacology (12.3)]. Hepatic accumulation of copper and manganese has been reported with long-term administration of parenteral nutrition at dosages higher than recommended [see Warnings and Precautions (5.4)].

For patients with cholestasis or cirrhosis, monitor hepatic and biliary function during long-term administration of Multrys.

If a patient develops signs or symptoms of hepatobiliary disease during use of Multrys, obtain serum concentrations of copper and ceruloplasmin as well as manganese whole blood concentrations; consider using individual trace element products in these patients.

10 OVERDOSAGE

There is no information on overdose-related toxicity with a fixed-combination trace element product. However, there are reports on overdosage in the literature for the individual trace elements. Management of overdosage is supportive care based on presenting signs and symptoms. Obtain blood samples for laboratory testing of the individual trace elements and ceruloplasmin for copper.

Zinc

Acute zinc toxicity was reported in an infant who received an inadvertent 1,000-fold overdose of zinc in parenteral nutrition that led to cardiac failure and death. Zinc toxicity in adult patients receiving 17 to 400-fold the recommended dosage in parenteral nutrition for 2.5 to 60 days reported signs and symptoms including vomiting, diarrhea, hyperamylasemia, thrombocytopenia, and anemia. The zinc serum concentration was 2 to 30-fold the upper end of the reported range in healthy subjects in these cases.

Copper

Acute copper toxicity was reported in patients with oral, intravenous, or subcutaneous administration. Clinical manifestations included metallic taste, nausea, vomiting, abdominal pain, and multi-organ failure involving kidney, liver, blood, and cardiovascular systems. Chelating agents can be used for treatment of acute toxicity. Long-term administration of parenteral copper above recommended dosage may result in significant accumulation of copper in the liver, brain, and other tissues with possible organ damage [see Warnings and Precautions (5.4)].

Manganese

Acute manganese toxicity was reported in adult patients following infusion of manganese more than 10,000-fold the recommended dosage and after use of dialysis fluid contaminated with manganese. Signs and symptoms included skin flushing, acute pancreatitis, elevated whole blood manganese concentrations, and MRI evidence of brain accumulation of manganese. Chronic infusion and oral intake of manganese above recommended dosage have resulted in neuropsychiatric symptoms and MRI evidence of brain accumulation of manganese [see Warnings and Precautions (5.3)].

Selenium

Acute selenium toxicity was reported with oral overdosage of greater than 1 g/day. Symptoms included nausea, vomiting, diarrhea, abdominal pain, garlic breath odor, and altered mental status. Death from circulatory collapse was reported after oral ingestion of 5 to 10 g of selenium with blood concentrations ranging 10 to 50-fold the upper end of the reported range in healthy subjects.

11 DESCRIPTION

Multrys (trace elements injection 4*, USP) is a sterile, non-pyrogenic, clear, and colorless to slightly blue solution, intended for use as a combination of four trace elements and an additive to intravenous solutions for parenteral nutrition. It contains no preservative.

Each single-dose vial contains 1 mL. *Each mL contains zinc 1,000 mcg (equivalent to zinc sulfate 2,470 mcg), copper 60 mcg (equivalent to cupric sulfate 150 mcg), manganese 3 mcg (equivalent to manganese sulfate 8.22 mcg), selenium 6 mcg (equivalent to selenious acid 9.8 mcg), and water for injection. Sulfuric acid may be added to adjust pH between 1.5 and 3.5.

Zinc sulfate exists as a heptahydrate. The structural formula is:

Molecular formula: ZnSO4 • 7H2O.
Molecular weight: 287.54 g/mol.

Cupric sulfate exists as a pentahydrate. The structural formula is:

Molecular formula: CuSO4 • 5H2O.
Molecular weight: 249.69 g/mol.

Manganese sulfate exists as a monohydrate. The structural formula is:

Molecular formula: MnSO4 • H2O.

Molecular weight: 169.02 g/mol.

The structural formula of selenious acid is:

Molecular formula: H2SeO3.
Molecular weight: 128.97 g/mol.

Multrys contains no more than 1,500 mcg/L of aluminum.

12 CLINICAL PHARMACOLOGY

12.1 Mechanism of Action

Zinc

Zinc functions as a cofactor of various enzymes including DNA polymerases, RNA polymerases, alcohol dehydrogenase, and alkaline phosphatases. Zinc is a coordinator of protein structural folding that interacts with a variety of proteins, lipids, and nucleic acids. In addition, zinc is a catalyst of essential biochemical reactions, including activation of substrates of carbonic anhydrase in erythrocyte.

Copper

Copper is a cofactor for many metalloenzymes acting as an oxidase to achieve reduction of molecular oxygen. Examples of copper metalloenzymes include but are not limited to lysyl oxidase, monoamine oxidase, ferroxidase, cytochrome C oxidase, dopamine beta monooxygenase, tyrosinase, and superoxide dismutase.

Manganese

Manganese is essential for the normal catalytic activity of several metalloenzymes including manganese superoxide dismutase, arginase, glutamine synthetase, phosphoenolpyruvate decarboxylase, and pyruvate carboxylase. Manganese contributes to the normal function of several other enzyme families including the oxidoreductases, transferases, hydrolases, lyases, isomerases, and ligases.

Selenium

Selenious acid is converted in vivo to hydrogen selenide via glutathione-involved electron reductions. Hydrogen selenide acts as a selenium pool to form selenoproteins which include, but are not limited to, glutathione peroxidase, iodothyronine deiodinase, peroxidase, and thioredoxins.

12.2 Pharmacodynamics

The exposure-response relationship and the time course of pharmacodynamic response are unknown for zinc, copper, manganese, and selenium.

12.3 Pharmacokinetics

Zinc

Over 85% of total body zinc is found in skeletal muscle and bone. In blood, zinc is mainly localized within erythrocytes. Approximately 80% of serum zinc is bound to albumin and the remainder to α-2-macroglobulin and amino acids. In adults, zinc is primarily excreted via the gastrointestinal tract and eliminated in the feces. A smaller amount of zinc is excreted via the kidneys in the urine. Urinary zinc excretion rates in very low birth weight preterm infants are relatively high in the neonatal period, and they decline to a level on a body weight basis that is similar to that of normal adults by two months of age.

Copper

In plasma, about 7% of copper is bound to albumin and amino acids. In the liver, about 93% of copper is bound to ceruloplasmin and released to the serum. Copper is excreted in bile and into the gastrointestinal tract where it is not reabsorbed. Copper is also eliminated through the kidneys.

Manganese

Manganese is widely distributed in body tissues including liver and specific brain regions such as the basal ganglia. The concentrations of manganese are higher in erythrocytes compared to the plasma or serum concentrations. In human plasma, manganese is bound to albumin and β1-globulin. Manganese is found in human bile suggesting biliary excretion.

Selenium

In humans, 85% of intravenous administered ^75Se-sodium selenite was protein-bound within 4 to 6 hours and 95% by 24 hours.

16 HOW SUPPLIED

Multrys (trace elements injection 4*, USP) is a clear, colorless to slightly blue solution supplied in:

- 1 mL single-dose vial (NDC 0517-9302-01) and packaged in trays containing 25 vials per tray (NDC 0517-9302-25).

*Each mL of Multrys contains zinc 1,000 mcg, copper 60 mcg, manganese 3 mcg, and selenium 6 mcg.

Vial closure is not made with natural rubber latex.

Store at 20°C to 25°C (68°F to 77°F), excursions permitted to 15°C to 30°C (59°F to 86°F) [See USP Controlled Room Temperature].

Store admixed solution at 2ºC to 8ºC (36ºF to 46ºF) [see Dosage and Administration (2.3)].

17 PATIENT COUNSELING INFORMATION

Inform patients, caregivers, and home healthcare providers of the following risks of Multrys:

- Pulmonary embolism due to pulmonary vascular precipitates [see Warnings and Precautions (5.1)]
- Vein damage and thrombosis [see Warnings and Precautions (5.2)]
- Neurologic toxicity with manganese [see Warnings and Precautions (5.3)]
- Hepatic accumulation of copper and manganese [see Warnings and Precautions (5.4)]
- Aluminum toxicity [see Warnings and Precautions (5.5)]
- Hypersensitivity reactions with zinc and copper [see Warnings and Precautions (5.7)]

Distributed by:

IN9302

PRINCIPAL DISPLAY PANEL - Container Label

NDC 0517-9302-01
Rx Only
Multrys® (Trace Elements Injection 4*, USP)
*Each mL provides: zinc 1,000 mcg, copper 60 mcg, manganese 3 mcg, and selenium 6 mcg
For intravenous infusion after admixing

For use in neonatal and pediatric patients weighing less than 10 kg
1 mL Single-Dose Vial - Discard Unused Portion

PRINCIPAL DISPLAY PANEL - Carton Labeling

NDC 0517-9302-25
Rx Only
Multrys® (Trace Elements Injection 4*, USP)
*Each mL provides: zinc 1,000 mcg, copper 60 mcg, manganese 3 mcg, and selenium 6 mcg

For intravenous infusion after admixing

For use in neonatal and pediatric patients weighing less than 10 kg
25 x 1 mL Single-Dose Vials - Discard Unused Portion